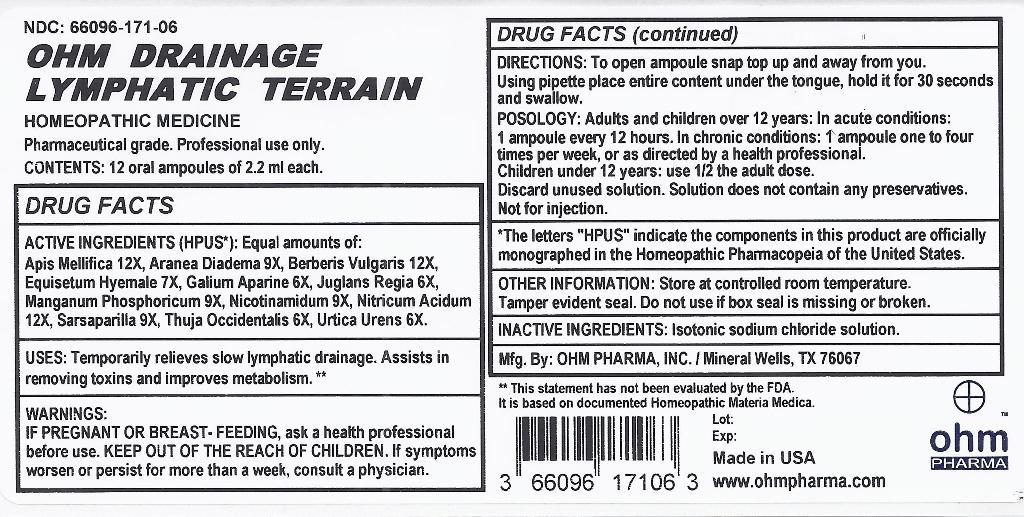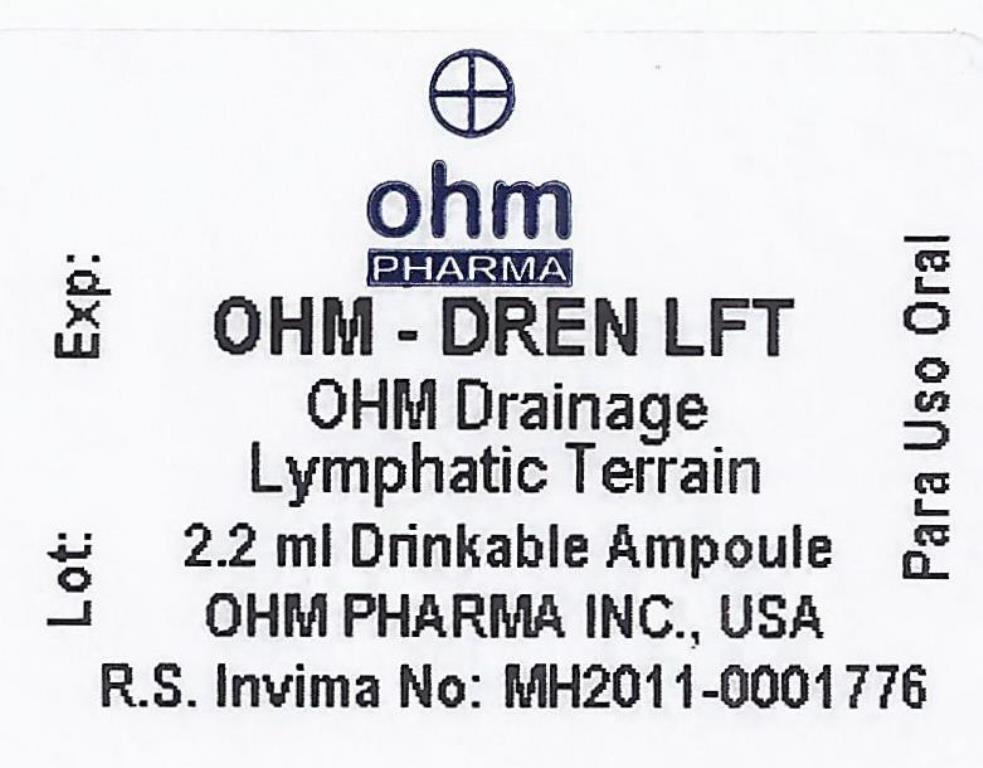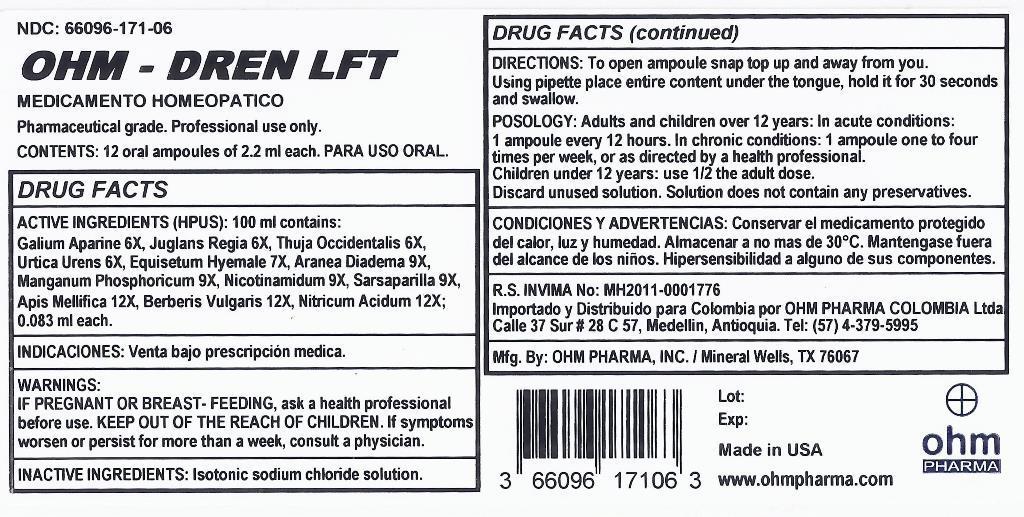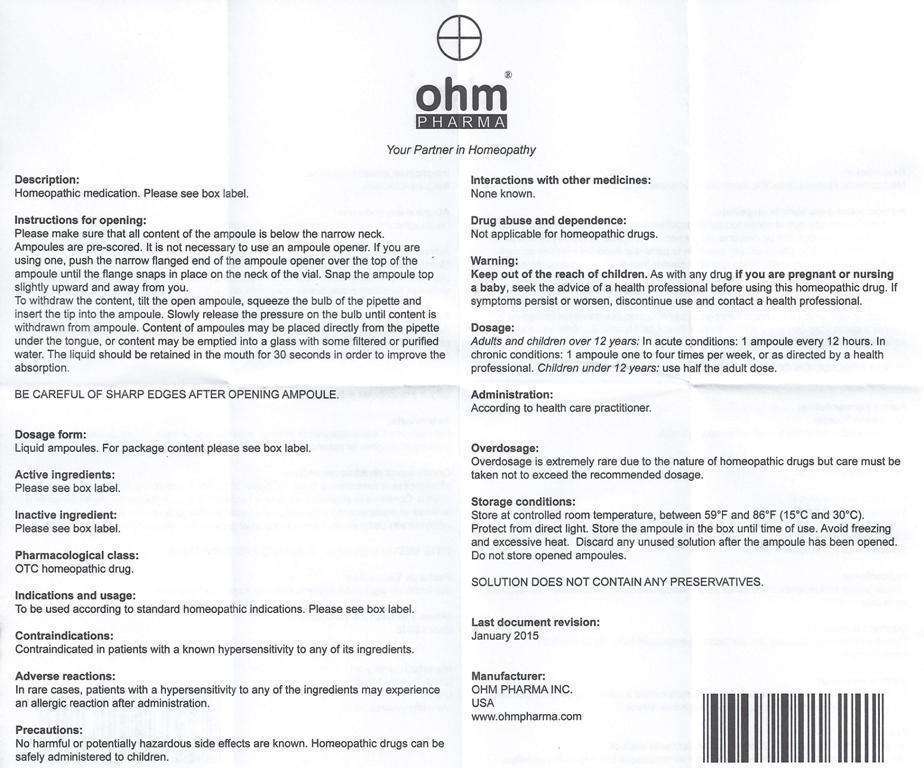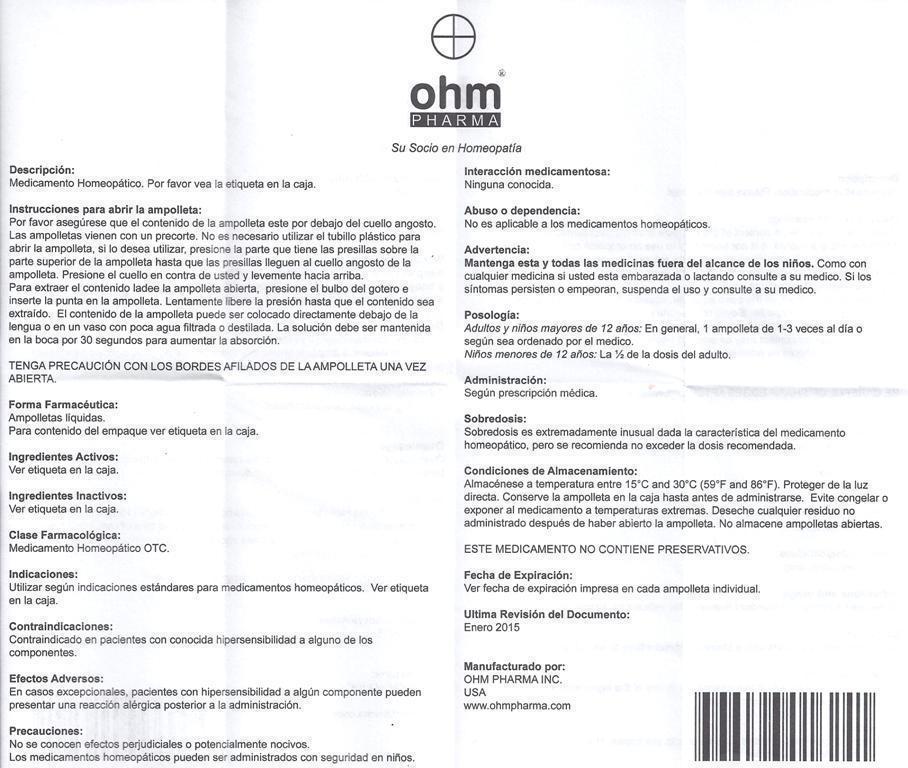 DRUG LABEL: OHM DRAINAGE LYMPHATIC TERRAIN
NDC: 66096-171 | Form: LIQUID
Manufacturer: OHM PHARMA INC.
Category: homeopathic | Type: HUMAN OTC DRUG LABEL
Date: 20160111

ACTIVE INGREDIENTS: APIS MELLIFERA 12 [hp_X]/1 mL; ARANEUS DIADEMATUS 9 [hp_X]/1 mL; BERBERIS VULGARIS ROOT BARK 12 [hp_X]/1 mL; EQUISETUM HYEMALE 7 [hp_X]/1 mL; GALIUM APARINE 6 [hp_X]/1 mL; JUGLANS REGIA WHOLE 6 [hp_X]/1 mL; MANGANESE PHOSPHATE, DIBASIC 9 [hp_X]/1 mL; NIACINAMIDE 9 [hp_X]/1 mL; NITRIC ACID 12 [hp_X]/1 mL; SMILAX REGELII ROOT 9 [hp_X]/1 mL; THUJA OCCIDENTALIS LEAFY TWIG 6 [hp_X]/1 mL; URTICA URENS 6 [hp_X]/1 mL
INACTIVE INGREDIENTS: SODIUM CHLORIDE

OHM DRAINAGE LYMPHATIC TERRAIN

ACTIVE INGREDIENT

ACTIVE INGREDIENTS (HPUS*): Equal amounts of: Apis Mellifica 12X, Aranea Diadema 9X, Berberis Vulgaris 12X, Equisetum Hyemale 7X, Galium Aparine 6X, Juglans Regia 6X, Manganum Phosphoricum 9X, Nicotinamidum 9X, Nitricum Acidum12X, Sarsaparilla 9X, Thuja Occidentalis 6X, Urtica Urens 6X.

ACTIVE INGREDIENT

*The letters "HPUS" indicate the components in this product are officially monographed in the Homeopathic Pharmacopeia of the United States.

INDICATIONS AND USAGE

USES: Temporarily relieves slow lymphatic drainage. Assists in removing toxins and improves metabolism.**

**This statement has not been evaluated by the FDA.
It is based on documented Homeopathic Materia Medica.

WARNINGS:

IF PREGNANT OR BREAST-FEEDING, ask a health professional before use. If symptoms worsen or persist for more than a week, consult a physician.

KEEP OUT OF THE REACH OF CHILDREN.

DOSAGE AND ADMINISTRATION

DIRECTIONS: To open ampoule snap top up and away from you. Using pipette place entire content under the tongue, hold it for 30 seconds and swallow.

POSOLOGY: Adults and children over 12 years: In acute conditions: 1 ampoule every 12 hours. In chronic conditions: 1 ampoule one to four times per week, or as directed by a health professional.

Children under 12 years use 1/2 the adult dose.

Discard unused solution. Solution does not contain any preservatives.

Not for injection.

OTHER INFORMATION: Store at controlled room temperature. Tamper evident seal. Do not use if box seal is missing or broken.

INACTIVE INGREDIENTS: Isotonic sodium chloride solution.

QUESTIONS

Mfg. By: OHM PHARMA, INC. / Mineral Wells, TX 76067

Made in USA

www.ohmpharma.com

PURPOSE

Slow lymphatic drainage relief

PACKAGE LABEL

NDC: 66096-171-06

OHM DRAINAGE LYMPHATIC TERRAIN

HOMEOPATHIC MEDICINE

Pharmaceutical Grade. Professional use only.

CONTENTS: 12 oral ampoules of 2.2 ml each.